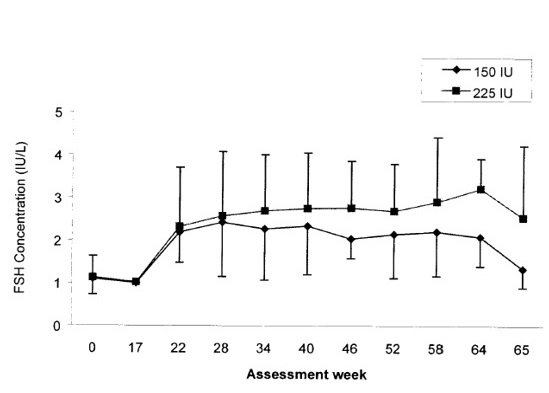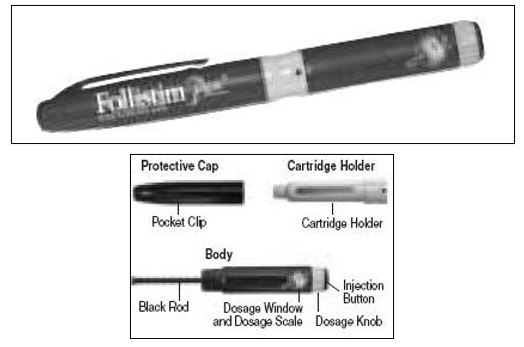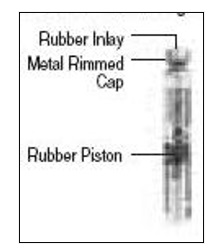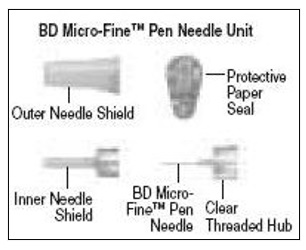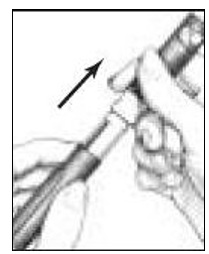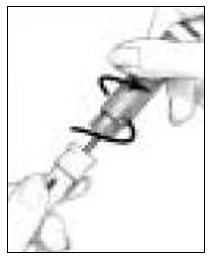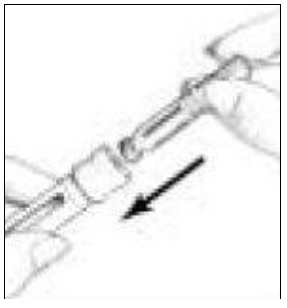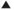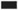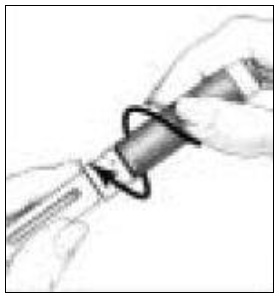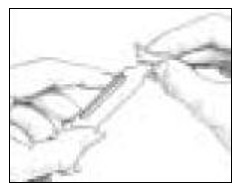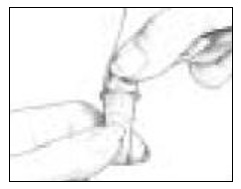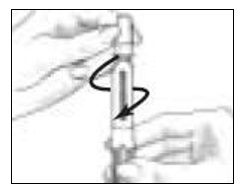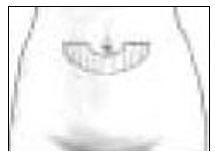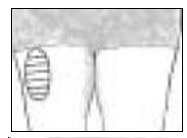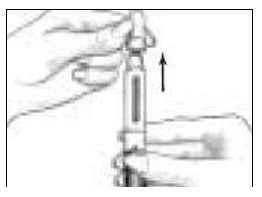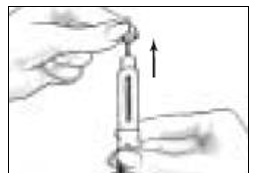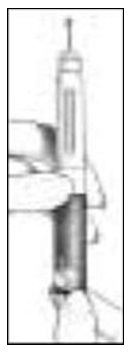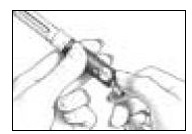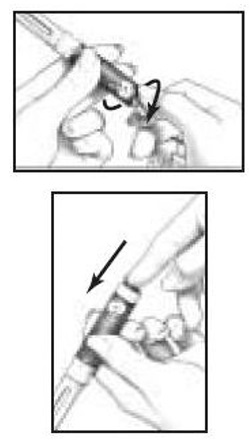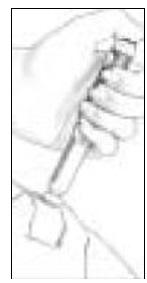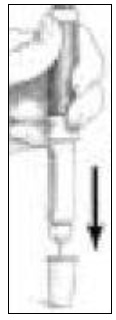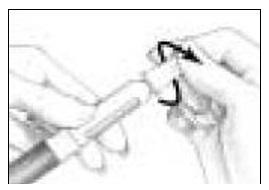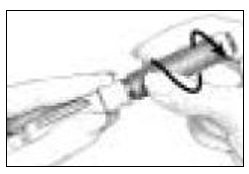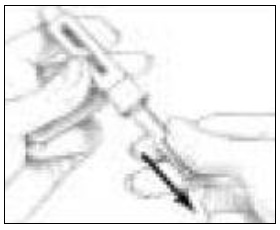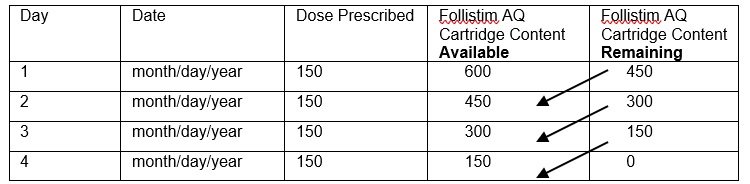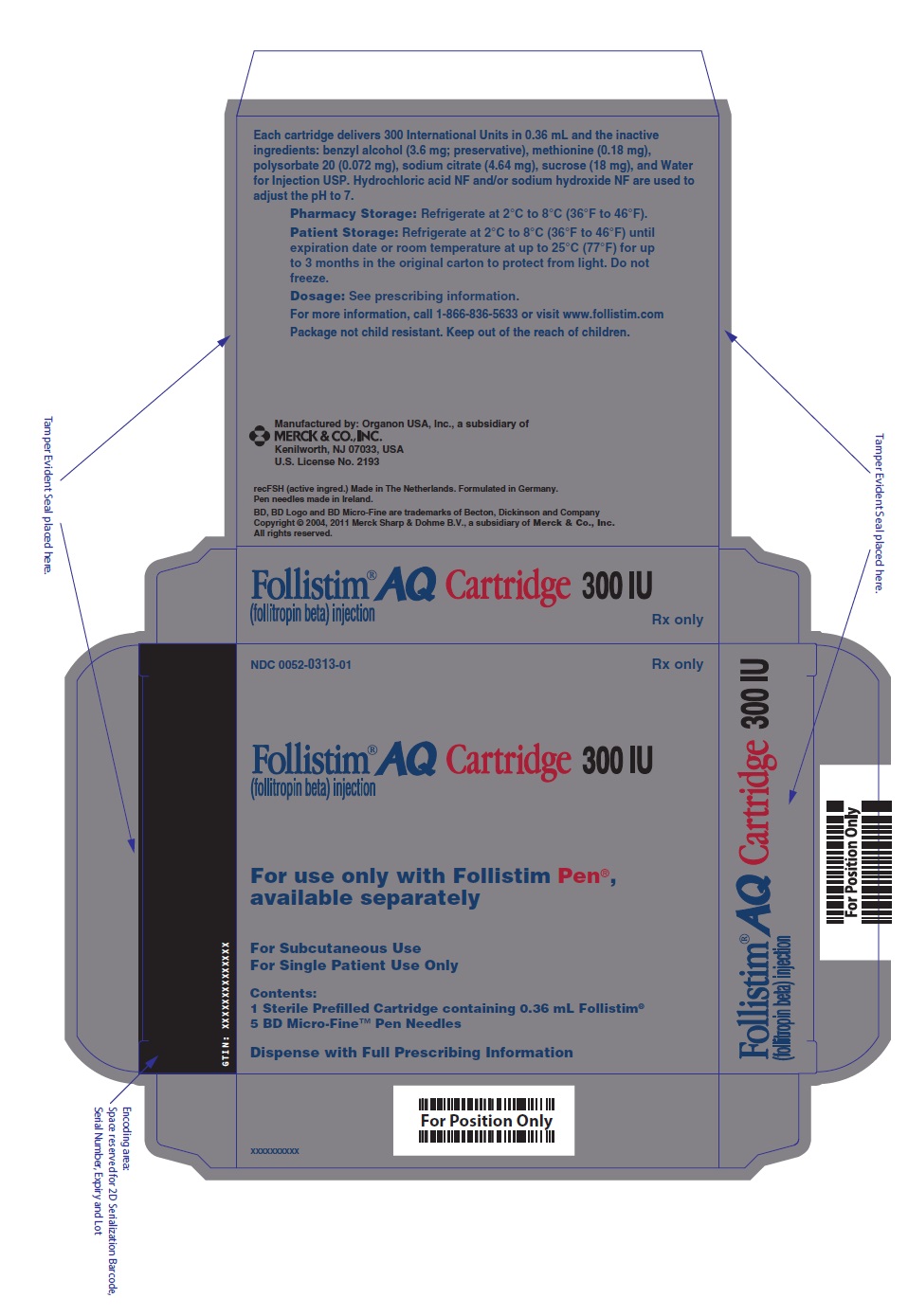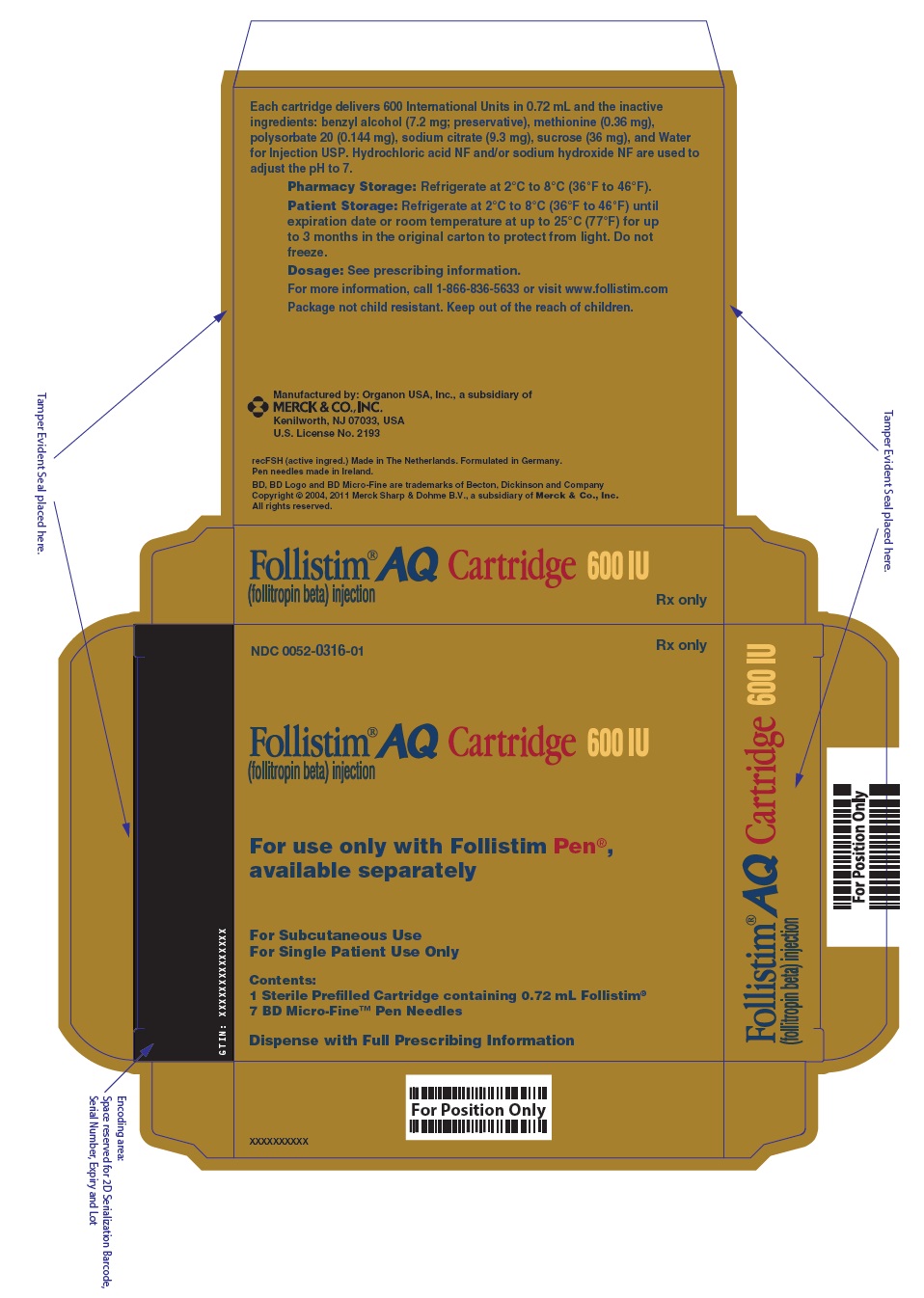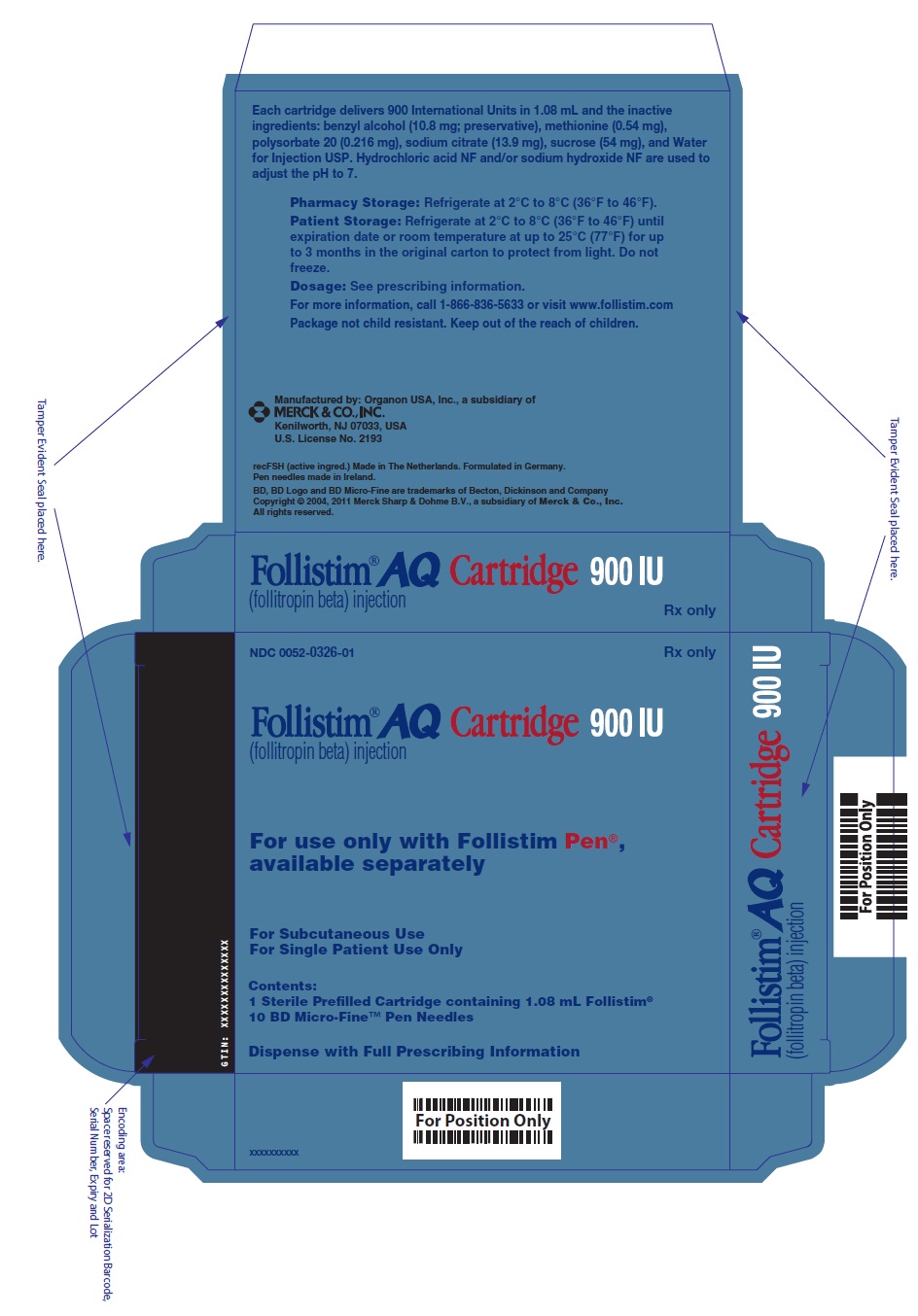 DRUG LABEL: Follistim AQ
NDC: 0052-0313 | Form: INJECTION, SOLUTION
Manufacturer: Merck Sharp & Dohme LLC
Category: prescription | Type: HUMAN PRESCRIPTION DRUG LABEL
Date: 20251003

ACTIVE INGREDIENTS: follitropin 350 [iU]/0.42 mL
INACTIVE INGREDIENTS: benzyl alcohol; methionine; polysorbate 20; trisodium citrate dihydrate; sucrose; water; hydrochloric acid; sodium hydroxide

HIGHLIGHTS OF PRESCRIBING INFORMATION

These highlights do not include all the information needed to use FOLLISTIM AQ Cartridge safely and effectively. See full prescribing information for FOLLISTIM AQ Cartridge.
FOLLISTIM® AQ Cartridge (follitropin beta) injection, for subcutaneous use
Initial U.S. Approval: 1997

1 INDICATIONS AND USAGE

Follistim AQ Cartridge is a gonadotropin indicated:

In Women for:

- Induction of Ovulation and Pregnancy in Anovulatory Infertile Women in Whom the Cause of Infertility is Functional and Not Due to Primary Ovarian Failure (1.1)
- Pregnancy in Normal Ovulatory Women Undergoing Controlled Ovarian Stimulation as Part of an In Vitro Fertilization (IVF) or Intracytoplasmic Sperm Injection (ICSI) Cycle (1.2)

In Men for:

- Induction of Spermatogenesis in Men with Primary and Secondary Hypogonadotropic Hypogonadism (HH) in Whom the Cause of Infertility is Not Due to Primary Testicular Failure (1.3)

2 DOSAGE AND ADMINISTRATION

See Dose Conversion Table 1 for Follistim AQ Cartridge with Pen Injector (2.1)

In Anovulatory Women Undergoing Ovulation Induction (2.2):

- Starting daily dose of 50 international units of Follistim AQ Cartridge is administered subcutaneously for at least the first 7 days. The dose is increased by 25 or 50 international units at weekly intervals until follicular growth and/or serum estradiol levels indicate an adequate response.
  - When an acceptable pre-ovulatory state is achieved, final oocyte maturation is achieved with 5,000 to 10,000 international units of urinary human chorionic gonadotropin (hCG).
  - The woman and her partner should have intercourse daily, beginning on the day prior to the administration of hCG and until ovulation becomes apparent.

In Normal Ovulatory Women Undergoing Controlled Ovarian Stimulation as Part of an In Vitro Fertilization or Intracytoplasmic Sperm Injection Cycle (2.3):

- Starting dose of 200 international units (actual cartridge doses) of Follistim AQ Cartridge is administered subcutaneously for at least the first 7 days of treatment. Subsequent doses can be adjusted down or up based upon ovarian response as determined by ultrasound evaluation of follicular growth and serum estradiol levels. Dosage reduction in high responders can be considered from the 6th day of treatment onward according to individual response.
  - Final oocyte maturation is induced with a dose of 5,000-10,000 international units of urinary hCG.
  - Oocyte (egg) retrieval is performed 34 to 36 hours later.

Induction of Spermatogenesis in Men (2.4):

- Pretreatment with urinary hCG alone (1,500 international units twice weekly) is required. If serum testosterone levels have not normalized after 8 weeks of hCG treatment, the dose may be increased to 3,000 international units twice a week.
- After normalization of serum testosterone levels, administer 450 international units per week (225 international units twice weekly or 150 international units three times weekly) of Follistim AQ Cartridge subcutaneously with the same pre-treatment hCG dose used to normalize testosterone levels.

3 DOSAGE FORMS AND STRENGTHS

Injection: Follistim AQ Cartridge 300 International Units per 0.36 mL in a single-patient-use cartridge (3)

Injection: Follistim AQ Cartridge 600 International Units per 0.72 mL in a single-patient-use cartridge (3)

Injection: Follistim AQ Cartridge 900 International Units per 1.08 mL in a single-patient-use cartridge (3)

4 CONTRAINDICATIONS

Women and men who exhibit:

- Prior hypersensitivity to recombinant hFSH products (4)
- High levels of FSH indicating primary gonadal failure (4)
- Presence of uncontrolled non-gonadal endocrinopathies (4)
- Hypersensitivity reactions related to streptomycin or neomycin (4)
- Tumors of the ovary, breast, uterus, testis, hypothalamus or pituitary gland (4)

Women who exhibit:

- Pregnancy (4, 8.1)
- Heavy or irregular vaginal bleeding of undetermined origin (4)
- Ovarian cysts or enlargement not due to polycystic ovary syndrome (PCOS) (4)

5 WARNINGS AND PRECAUTIONS

Treatment with Follistim AQ may result in:

- Abnormal Ovarian Enlargement (5.1)
- Ovarian Hyperstimulation Syndrome (OHSS) (5.2)
- Pulmonary and Vascular Complications (5.3)
- Ovarian Torsion (5.4)
- Multi-fetal Gestation and Birth (5.5)
- Congenital Anomalies (5.6)
- Ectopic Pregnancy (5.7)
- Spontaneous Abortion (5.8)
- Ovarian Neoplasms (5.9)

6 ADVERSE REACTIONS

The most common adverse reactions (≥2%) in women undergoing ovulation induction are ovarian hyperstimulation syndrome, ovarian cyst, abdominal discomfort, abdominal pain and lower abdominal pain. (6.1)

The most common adverse reactions (≥2%) in women undergoing controlled ovarian stimulation as part of an IVF or ICSI cycle are pelvic discomfort, headache, ovarian hyperstimulation syndrome, pelvic pain, nausea and fatigue. (6.1)

The most common (≥2%) adverse reactions in men undergoing induction of spermatogenesis are headache, acne, injection site reaction, injection site pain, gynecomastia, rash and dermoid cyst. (6.1)

To report SUSPECTED ADVERSE REACTIONS, contact Merck Sharp & Dohme Corp., a subsidiary of Merck & Co., Inc., at 1-877-888-4231 or FDA at 1-800-FDA-1088 or www.fda.gov/medwatch.

8 USE IN SPECIFIC POPULATIONS

Lactation: It is not known whether this drug is excreted in human milk. (8.2)

FULL PRESCRIBING INFORMATION

1 INDICATIONS AND USAGE

Follistim® AQ Cartridge (follitropin beta) injection, is indicated:

In Women for:

1.1 Induction of Ovulation and Pregnancy in Anovulatory Infertile Women in Whom the Cause of Infertility is Functional and Not Due to Primary Ovarian Failure

Prior to initiation of treatment with Follistim AQ Cartridge:

- Women should have a complete gynecologic and endocrinologic evaluation.
- Primary ovarian failure should be excluded.
- The possibility of pregnancy should be excluded.
- Tubal patency should be demonstrated.
- The fertility status of the male partner should be evaluated.

1.2 Pregnancy in Normal Ovulatory Women Undergoing Controlled Ovarian Stimulation as Part of an In Vitro Fertilization (IVF) or Intracytoplasmic Sperm Injection (ICSI) Cycle

Prior to initiation of treatment with Follistim AQ Cartridge:

- Women should have a complete gynecologic and endocrinologic evaluation and diagnosis of cause of infertility.
- The possibility of pregnancy should be excluded.
- The fertility status of the male partner should be evaluated.

In Men for:

1.3 Induction of Spermatogenesis in Men with Primary and Secondary Hypogonadotropic Hypogonadism (HH) in Whom the Cause of Infertility is Not Due to Primary Testicular Failure

Prior to initiation of treatment with Follistim AQ Cartridge:

- Men should have a complete medical and endocrinologic evaluation.
- Hypogonadotropic hypogonadism should be confirmed and primary testicular failure should be excluded.
- Serum testosterone levels should be normalized with human chorionic gonadotropin (hCG) treatment.
- The fertility status of the female partner should be evaluated.

2 DOSAGE AND ADMINISTRATION

2.1 General Dosing Information

- Parenteral drug products should be inspected visually for particulate matter and discoloration prior to administration, whenever solution and container permit. If the solution is not clear and colorless or has particles in it, the solution should not be used.
- Do not add any other medicines into the Follistim AQ Cartridge.
- Follistim AQ Cartridge with the pen injector device delivers on average an 18% higher amount of follitropin beta when compared to reconstituted Follistim delivered with a conventional syringe and needle. When administering Follistim AQ Cartridge, a lower starting dose and lower dose adjustments (as compared to reconstituted Follistim) should be considered. For that purpose the following Dose Conversion Table is provided:

Table 1: Follistim AQ Cartridge Administered Subcutaneously with the Follistim Pen Dose Conversion Table [Each value represents an 18% difference rounded to the nearest 25 IU increment.]
Lyophilized recombinant FSH dosing with ampules or vials, using conventional syringe | Follistim AQ Cartridge dosing with the Follistim Pen
75 IU | 50 IU
150 IU | 125 IU
225 IU | 175 IU
300 IU | 250 IU
375 IU | 300 IU
450 IU | 375 IU

2.2 Recommended Dosing in Anovulatory Women Undergoing Ovulation Induction

The dosing scheme is stepwise and is individualized for each woman [see Clinical Studies (14.1)].

- A starting daily dose of 50 international units of Follistim AQ Cartridge is administered [see Dosage and Administration (2.1)] subcutaneously daily for at least the first 7 days.
- Subsequent dosage adjustments are made at weekly intervals based upon ovarian response. If an increase in dose is indicated by the ovarian response, the increase should be made by 25 or 50 international units of Follistim AQ Cartridge at weekly intervals until follicular growth and/or serum estradiol levels indicate an adequate ovarian response.
  The following should be considered when planning the woman's individualized dose:
  - Appropriate Follistim AQ Cartridge dose adjustment(s) should be used to prevent multiple follicular growth and cycle cancellation.
  - The maximum, individualized, daily dose of Follistim AQ Cartridge is 250 international units.
- Treatment should continue until ultrasonic visualizations and/or serum estradiol determinations approximate the pre-ovulatory conditions seen in normal individuals.
- When pre-ovulatory conditions are reached, 5,000 to 10,000 international units of urinary hCG are used to induce final oocyte maturation and ovulation.
  The administration of hCG must be withheld in cases where the ovarian monitoring suggests an increased risk of OHSS on the last day of Follistim AQ Cartridge therapy [see Warnings and Precautions (5.1, 5.2, 5.10)].
- The woman and her partner should be encouraged to have intercourse daily, beginning on the day prior to the administration of hCG and until ovulation becomes apparent [see Warnings and Precautions (5.10)].
- During treatment with Follistim AQ Cartridge and during a two-week post-treatment period, the woman should be assessed at least every other day for signs of excessive ovarian stimulation.
  It is recommended that Follistim AQ Cartridge administration be stopped if the ovarian monitoring suggests an increased risk of OHSS or abdominal pain occurs. Most OHSS occurs after treatment has been discontinued and reaches its maximum at about seven to ten days post-ovulation.

2.3 Recommended Dosing in Normal Ovulatory Women Undergoing Controlled Ovarian Stimulation as Part of an In Vitro Fertilization (IVF) or Intracytoplasmic Sperm Injection (ICSI) Cycle

The dosing scheme follows a stepwise approach and is individualized for each woman.

- A starting dose of 200 international units (actual cartridge doses) of Follistim AQ Cartridge is administered [see Dosage and Administration (2.1)] subcutaneously daily for at least the first 7 days of treatment.
- Subsequent to the first 7 days of treatment, the dose can be adjusted down or up based upon the woman's ovarian response as determined by ultrasound evaluation of follicular growth and serum estradiol levels. Dosage reduction in high responders can be considered from the 6th day of treatment onward according to individual response.
  The following should be considered when planning the woman's individualized dose:
  - For most normal responding women, the daily starting dose can be continued until pre-ovulatory conditions are achieved (seven to twelve days).
  - For low or poor responding women, the daily dose should be increased according to the ovarian response. The maximum, individualized, daily dose of Follistim AQ Cartridge is 500 international units.
  - For high responding women [those at particular risk of abnormal ovarian enlargement and/or ovarian hyperstimulation syndrome (OHSS)], decrease or temporarily stop the daily dose, or discontinue the cycle according to individual response [see Warnings and Precautions (5.1, 5.2, 5.10)].
- When a sufficient number of follicles of adequate size are present, dosing of Follistim AQ Cartridge is stopped and final maturation of the oocytes is induced by administering urinary hCG at a dose of 5,000 to 10,000 international units. The administration of hCG should be withheld in cases where the ovarian monitoring suggests an increased risk of OHSS on the last day of Follistim AQ Cartridge therapy [see Warnings and Precautions (5.1, 5.2, 5.10)].
- Oocyte (egg) retrieval should be performed 34 to 36 hours following the administration of hCG.

2.4 Recommended Dosing for Induction of Spermatogenesis in Men

- Pretreatment with hCG is required prior to concomitant therapy with Follistim AQ Cartridge and hCG. An initial dosage of 1,500 international units of urinary hCG should be administered at twice weekly intervals to normalize serum testosterone levels. If serum testosterone levels have not normalized after 8 weeks of hCG treatment, the urinary hCG dose can be increased to 3,000 international units twice weekly [see Clinical Studies (14.3)].
- After normal serum testosterone levels have been reached, Follistim AQ Cartridge should be administered by subcutaneous injection concomitantly with hCG treatment. Follistim is given at a dosage of 450 international units per week, as either 225 international units twice weekly or 150 international units three times per week, in combination with the same hCG dose used to normalize testosterone levels. Based on delivery of a higher dose of follitropin beta with the Follistim AQ Cartridge and pen injector [see Dosage and Administration (2.1)], a lower dose of Follistim AQ Cartridge may be considered.
  The concomitant therapy should be continued for at least 3 to 4 months before any improvement in spermatogenesis can be expected. If a man has not responded after this period, the combination therapy may be continued. Treatment response has been noted at up to 12 months.

3 DOSAGE FORMS AND STRENGTHS

Follistim AQ Cartridge is a clear and colorless solution available as:

Injection: 300 international units per 0.36 mL in a single-patient-use cartridge

Injection: 600 international units per 0.72 mL in a single-patient-use cartridge

Injection: 900 international units per 1.08 mL in a single-patient-use cartridge

4 CONTRAINDICATIONS

Follistim AQ Cartridge is contraindicated in women and men who exhibit:

- Prior hypersensitivity to recombinant hFSH products
- High levels of FSH indicating primary gonadal failure
- Presence of uncontrolled non-gonadal endocrinopathies (e.g., thyroid, adrenal, or pituitary disorders) [see Indications and Usage (1.1, 1.2, 1.3)]
- Hypersensitivity reactions to streptomycin or neomycin. Follistim AQ may contain traces of these antibiotics
- Tumors of the ovary, breast, uterus, testis, hypothalamus or pituitary gland

Follistim AQ Cartridge is also contraindicated in women who exhibit:

- Pregnancy [see Use in Specific Populations (8.1)]
- Heavy or irregular vaginal bleeding of undetermined origin
- Ovarian cysts or enlargement not due to polycystic ovary syndrome (PCOS)

5 WARNINGS AND PRECAUTIONS

Follistim AQ Cartridge should be used only by physicians who are experienced in infertility treatment. Follistim AQ Cartridge contains a potent gonadotropic substance capable of causing Ovarian Hyperstimulation Syndrome (OHSS) [see Warnings and Precautions (5.2)] with or without pulmonary or vascular complications [see Warnings and Precautions (5.3)] and multiple births [see Warnings and Precautions (5.5)]. Gonadotropin therapy requires the availability of appropriate monitoring facilities [see Warnings and Precautions (5.10)].

Careful attention should be given to the diagnosis of infertility and in the selection of candidates for Follistim AQ Cartridge therapy [see Indications and Usage (1.1, 1.2, 1.3) and Dosage and Administration (2.2, 2.3, 2.4)].

Switching to Follistim AQ Cartridge from other brands (manufacturer), types (recombinant, urinary), and/or methods of administration (Follistim Pen, conventional syringe) may necessitate an adjustment of the dose [see Dosage and Administration (2)].

5.1 Abnormal Ovarian Enlargement

In order to minimize the hazards associated with abnormal ovarian enlargement that may occur with Follistim AQ therapy, treatment should be individualized and the lowest effective dose should be used [see Dosage and Administration (2.2, 2.3)]. Use of ultrasound monitoring of ovarian response and/or measurement of serum estradiol levels is important to minimize the risk of overstimulation [see Warnings and Precautions (5.8)].

If the ovaries are abnormally enlarged on the last day of Follistim AQ therapy, hCG should not be administered in order to reduce the chances of developing Ovarian Hyperstimulation Syndrome (OHSS). Intercourse should be prohibited in patients with significant ovarian enlargement after ovulation because of the danger of hemoperitoneum resulting from ruptured ovarian cysts [see Warnings and Precautions (5.3)].

5.2 Ovarian Hyperstimulation Syndrome (OHSS)

OHSS is a medical entity distinct from uncomplicated ovarian enlargement and may progress rapidly to become a serious medical condition. OHSS is characterized by a dramatic increase in vascular permeability, which can result in a rapid accumulation of fluid in the peritoneal cavity, thorax, and potentially, the pericardium. The early warning signs of OHSS developing are severe pelvic pain, nausea, vomiting, and weight gain. Abdominal pain, abdominal distension, gastrointestinal symptoms including nausea, vomiting and diarrhea, severe ovarian enlargement, weight gain, dyspnea, and oliguria have been reported with OHSS. Clinical evaluation may reveal hypovolemia, hemoconcentration, electrolyte imbalances, ascites, hemoperitoneum, pleural effusions, hydrothorax, acute pulmonary distress, and thromboembolic reactions [see Warnings and Precautions (5.3)]. Transient liver function test abnormalities suggestive of hepatic dysfunction with or without morphologic changes on liver biopsy have also been reported in association with OHSS.

OHSS occurs after gonadotropin treatment has been discontinued, and it can develop rapidly, reaching its maximum about seven to ten days following treatment. Usually, OHSS resolves spontaneously with the onset of menses. If there is a risk for OHSS evident prior to hCG administration [see Warnings and Precautions (5.1)], the hCG must be withheld. Cases of OHSS are more common, more severe, and more protracted if pregnancy occurs; therefore, women should be assessed for the development of OHSS for at least two weeks after hCG administration.

If serious OHSS occurs, gonadotropins, including hCG, should be stopped and consideration should be given as to whether the patient needs to be hospitalized. Treatment is primarily symptomatic and overall should consist of bed rest, fluid and electrolyte management, and analgesics (if needed). Because the use of diuretics can accentuate the diminished intravascular volume, diuretics should be avoided except in the late phase of resolution as described below. The management of OHSS may be divided into three phases as follows:

- Acute Phase:
  Management should be directed at preventing hemoconcentration due to loss of intravascular volume to the third space and minimizing the risk of thromboembolic phenomena and kidney damage. Fluid intake and output, weight, hematocrit, serum and urinary electrolytes, urine specific gravity, BUN and creatinine, total proteins with albumin: globulin ratio, coagulation studies, electrocardiogram to monitor for hyperkalemia, and abdominal girth should be thoroughly assessed daily or more often based on the clinical need. Treatment, consisting of limited intravenous fluids, electrolytes, and human serum albumin is intended to normalize electrolytes while maintaining an acceptable but somewhat reduced intravascular volume. Full correction of the intravascular volume deficit may lead to an unacceptable increase in the amount of third space fluid accumulation.
- Chronic Phase:
  After the acute phase is successfully managed as above, excessive fluid accumulation in the third space should be limited by instituting severe potassium, sodium, and fluid restriction.
- Resolution Phase:
  As third space fluid returns to the intravascular compartment, a fall in hematocrit and increasing urinary output are observed in the absence of any increase in intake. Peripheral and/or pulmonary edema may result if the kidneys are unable to excrete third space fluid as rapidly as it is mobilized. Diuretics may be indicated during the resolution phase, if necessary, to combat pulmonary edema.

OHSS increases the risk of injury to the ovary. The ascitic, pleural, and pericardial fluid should not be removed unless there is the necessity to relieve symptoms such as pulmonary distress or cardiac tamponade. Pelvic examination may cause rupture of an ovarian cyst, which may result in hemoperitoneum, and should therefore be avoided. If bleeding occurs and requires surgical intervention, the clinical objective should be to control the bleeding and retain as much ovarian tissue as possible.

During clinical trials with Follistim or Follistim AQ Cartridge therapy, OHSS occurred in 7.6% of 105 women (OI) and 6.4% of 751 women (IVF or ICSI) treated with Follistim and Follistim AQ Cartridge, respectively.

5.3 Pulmonary and Vascular Complications

Serious pulmonary conditions (e.g., atelectasis, acute respiratory distress syndrome) have been reported in women treated with gonadotropins. In addition, thromboembolic reactions both in association with, and separate from OHSS have been reported following gonadotropin therapy. Intravascular thrombosis, which may originate in venous or arterial vessels, can result in reduced blood flow to vital organs or the extremities. Women with generally recognized risk factors for thrombosis, such as a personal or family history, severe obesity, or thrombophilia, may have an increased risk of venous or arterial thromboembolic events, during or following treatment with gonadotropins. Sequelae of such reactions have included venous thrombophlebitis, pulmonary embolism, pulmonary infarction, cerebral vascular occlusion (stroke), and arterial occlusion resulting in loss of limb and rarely in myocardial infarction. In rare cases, pulmonary complications and/or thromboembolic reactions have resulted in death. In women with recognized risk factors, the benefits of ovulation induction, in vitro fertilization (IVF) or intracytoplasmic sperm injection (ICSI) treatment need to be weighed against the risks. It should be noted that pregnancy itself also carries an increased risk of thrombosis.

5.4 Ovarian Torsion

Ovarian torsion has been reported after treatment with Follistim AQ Cartridge and after intervention with other gonadotropins. This may be related to OHSS, pregnancy, previous abdominal surgery, past history of ovarian torsion, previous or current ovarian cyst and polycystic ovaries. Damage to the ovary due to reduced blood supply can be limited by early diagnosis and immediate detorsion.

5.5 Multi-fetal Gestation and Birth

Multi-fetal gestation and births have been reported with all gonadotropin treatments including Follistim AQ Cartridge treatment. The woman and her partner should be advised of the potential risk of multi-fetal gestation and births before starting treatment.

5.6 Congenital Anomalies

The incidence of congenital malformations after IVF or ICSI may be slightly higher than after spontaneous conception. This slightly higher incidence is thought to be related to differences in parental characteristics (e.g., maternal age, sperm characteristics) and to the higher incidence of multi-fetal gestations after IVF or ICSI. There are no indications that the use of gonadotropins during IVF or ICSI is associated with an increased risk of congenital malformations.

5.7 Ectopic Pregnancy

Since infertile women undergoing IVF or ICSI often have tubal abnormalities, the incidence of ectopic pregnancies might be increased. Early confirmation of an intrauterine pregnancy should be determined by β-hCG testing and transvaginal ultrasound.

5.8 Spontaneous Abortion

The risk of spontaneous abortions (miscarriage) is increased with gonadotropin products. However, causality has not been established. The increased risk may be a factor of the underlying infertility.

5.9 Ovarian Neoplasms

There have been infrequent reports of ovarian neoplasms, both benign and malignant, in women who have undergone multiple drug regimens for controlled ovarian stimulation; however, a causal relationship has not been established.

5.10 Laboratory Tests

For Women:

In most instances, treatment with Follistim AQ Cartridge will result only in follicular growth and maturation. In order to complete the final phase of follicular maturation and to induce ovulation, hCG must be given following the administration of Follistim AQ Cartridge or when clinical assessment indicates that sufficient follicular maturation has occurred. The degree of follicular maturation and the timing of hCG administration can both be determined with the use of sonographic visualization of the ovaries and endometrial lining in conjunction with measurement of serum estradiol levels. The combination of transvaginal ultrasonography and measurement of serum estradiol levels is also useful for minimizing the risk of OHSS and multi-fetal gestations.

The clinical confirmation of ovulation is obtained by the following direct or indirect indices of progesterone production as well as sonographic evidence of ovulation.

Direct or indirect indices of progesterone production are:

- Urinary or serum luteinizing hormone (LH) rise
- A rise in basal body temperature
- Increase in serum progesterone
- Menstruation following the shift in basal body temperature

The following provide sonographic evidence of ovulation:

- Collapsed follicle
- Fluid in the cul-de-sac
- Features consistent with corpus luteum formation

Sonographic evaluation of the early pregnancy is also important to rule out ectopic pregnancy.

For Men:

Clinical monitoring for spermatogenesis utilizes the following indirect or direct measures:

- Serum testosterone level
- Semen analysis

5.11 Follistim Pen

The Follistim Pen is intended only for use with Follistim AQ Cartridge. The Follistim Pen is not recommended for the blind or visually impaired without the assistance of an individual with good vision who is trained in the proper use of the injection device.

6 ADVERSE REACTIONS

The following serious adverse reactions are discussed elsewhere in the labeling:

- Abnormal Ovarian Enlargement [see Warnings and Precautions (5.1)]
- Ovarian Hyperstimulation Syndrome [see Warnings and Precautions (5.2)]
- Atelectasis [see Warnings and Precautions (5.3)]
- Thromboembolism [see Warnings and Precautions (5.3)]
- Ovarian Torsion [see Warnings and Precautions (5.4)]
- Multi-fetal Gestation and Birth [see Warnings and Precautions (5.5)]
- Congenital Anomalies [see Warnings and Precautions (5.6)]
- Ectopic Pregnancy [see Warnings and Precautions (5.7)]
- Spontaneous Abortion [see Warnings and Precautions (5.8)]
- Ovarian Neoplasms [see Warnings and Precautions (5.9)]

6.1 Clinical Study Experience

Because clinical trials are conducted under widely varying conditions, adverse reactions rates observed in the clinical trials of a drug cannot be directly compared to rates in the clinical trial of another drug and may not reflect the rates observed in practice.

Ovulation Induction

In a single cycle, multi-center, assessor-blind, parallel group, comparative study, a total of 172 chronic anovulatory women who had failed to ovulate and/or conceive with clomiphene citrate therapy, were randomized and treated with Follistim (105) or a urofollitropin comparator. Adverse reactions with an incidence of greater than 2% in either treatment group are listed in Table 2.

Table 2: Common Adverse Reactions Reported at a Frequency of ≥2% in an Assessor-Blind, Comparative Study of Anovulatory Women Receiving Ovulation Induction
System Organ Class/Adverse Reactions | Treatment Number (%) of Women
System Organ Class/Adverse Reactions | Follistim N=105 n (%) | Comparator N=67 n (%)
Gastrointestinal disorders
Abdominal discomfort | 3 (2.9) | 1 (1.5)
Abdominal pain | 3 (2.9) | 2 (3.0)
Abdominal pain lower | 3 (2.9) | 1 (1.5)
Reproductive system and breast disorders
Ovarian cyst | 3 (2.9) | 2 (3.0)
Ovarian hyperstimulation syndrome | 8 (7.6) | 3 (4.5)
General disorders and administration site conditions
Pyrexia | 0 (0.0) | 2 (3.0)

Adverse reactions reported commonly (greater than or equal to 2% of women treated with Follistim) in other ovulation induction clinical trials were headache, abdominal distension, constipation, diarrhea, nausea, pelvic pain, uterine enlargement, vaginal hemorrhage and injection site reaction.

In Vitro Fertilization/Intracytoplasmic Sperm Injection

In a single cycle, multi-center, double-blind, parallel group, comparative study, a total of 1509 women were randomized to receive controlled ovarian stimulation with either Follistim AQ Cartridge (751 women were treated with Follistim AQ Cartridge) or a comparator and pituitary suppression with a gonadotropin releasing hormone (GnRH) antagonist as part of an in vitro fertilization (IVF) or intracytoplasmic sperm injection (ICSI) cycle. Table 3 lists adverse reactions with an incidence of greater than 2% in the group of women treated with Follistim AQ Cartridge.

Table 3: Common Adverse Reactions Reported at a Frequency of ≥2% in a Randomized, Double-blind, Active-controlled, Comparative Study of Normal Ovulatory Women Undergoing Controlled Ovarian Stimulation as Part of an In Vitro Fertilization or Intracytoplasmic Sperm Injection Cycle
System Organ Class/Adverse Reactions | Follistim AQ Cartridge Treatment N = 751 n [n = number of women with the adverse reaction] (%)
Nervous System disorders
Headache | 55 (7.3%)
Gastrointestinal disorders
Nausea | 29 (3.9%)
Reproductive system and breast disorders
Ovarian Hyperstimulation Syndrome | 48 (6.4%)
Pelvic discomfort | 62 (8.3%)
Pelvic Pain | 41 (5.5%)
General disorders and Administration site conditions
Fatigue | 17 (2.3%)

Induction of Spermatogenesis

In an open-label, non-comparative clinical trial, 49 men with hypogonadotropic hypogonadism were enrolled to receive pretreatment with hCG, followed by combination therapy with hCG and Follistim for induction of spermatogenesis. Of the 49 men, 30 received weekly Follistim doses of 450 international units; 24 of these 30 men received a total of 48 weeks of treatment with Follistim. Adverse reactions occurring with an incidence of greater than 2% in the 30 men treated with Follistim are listed in Table 4.

Table 4: Common Adverse Reactions Reported at a Frequency of ≥2% in an Open-Label Clinical Trial in Men with Hypogonadotropic Hypogonadism
System Organ Class/Adverse Reactions | Follistim Treatment N=30 n (%)
Nervous system disorders
Headache | 2 (6.7)
General disorders and administration site disorders
Injection site reaction | 2 (6.7)
Injection site pain | 2 (6.7)
Skin and cutaneous tissue disorders
Acne | 2 (6.7)
Rash | 1 (3.3)
Reproductive system and breast disorders
Gynecomastia | 1 (3.3)
Neoplasms benign, malignant and unspecified
Dermoid cyst | 1 (3.3)

6.2 Postmarketing Experience

The following adverse reactions have been identified during post-approval use of Follistim and/or Follistim AQ Cartridge. Because these reactions are reported voluntarily from a population of uncertain size, it is not always possible to reliably estimate their frequency or establish a causal relationship to drug exposure.

Gastrointestinal disorders
Abdominal distension, abdominal pain, constipation, diarrhea

General disorders and administration site conditions
Injection site reaction

Reproductive system and breast disorders
Breast tenderness, metrorrhagia, ovarian enlargement, vaginal hemorrhage

Skin and subcutaneous tissue disorders
Rash

Vascular disorders
Thromboembolism [see Warnings and Precautions (5.3)]

7 DRUG INTERACTIONS

No drug-drug interaction studies have been performed.

8 USE IN SPECIFIC POPULATIONS

8.1 Pregnancy

Risk Summary

Follistim AQ Cartridge is contraindicated for use in pregnant women and offers no benefit during pregnancy.

8.2 Lactation

Risk Summary

It is not known whether this drug is excreted in human milk. The developmental and health benefits of breastfeeding should be considered along with the mother’s clinical need for Follistim AQ Cartridge and any potential adverse effects on the breastfed child from Follistim AQ Cartridge or from the underlying maternal condition.

8.4 Pediatric Use

Follistim AQ Cartridge is not indicated for use in pediatric patients. Clinical studies have not been conducted in the pediatric population.

8.5 Geriatric Use

Clinical studies of Follistim AQ Cartridge have not been conducted in patients 65 years of age and older.

10 OVERDOSAGE

Aside from the possibility of Ovarian Hyperstimulation Syndrome [see Warnings and Precautions (5.2, 5.3)] and multiple gestations [see Warnings and Precautions (5.5)], there is no additional information concerning the consequences of acute overdosage with Follistim AQ Cartridge.

11 DESCRIPTION

Follitropin beta, a gonadotropin [human follicle-stimulating hormone (hFSH)], is a glycoprotein hormone produced by recombinant DNA technology in a Chinese hamster ovary (CHO) cell line. It has a dimeric structure containing two glycoprotein subunits (alpha and beta). The alpha and beta subunits have 92 and 111 amino acids, respectively, and their primary and tertiary structures are indistinguishable from that of hFSH. The molecular weight is approximately 40 kDa.

Follistim AQ Cartridge (follitropin beta) injection is a sterile clear and colorless solution, containing either 300 International Units, 600 International Units, or 900 International Units of follitropin beta in disposable single-patient-use cartridges for subcutaneous use only with the Follistim Pen.

Each cartridge delivers 300 International Units in 0.36 mL and the inactive ingredients: benzyl alcohol (3.6 mg; preservative), methionine (0.18 mg), polysorbate 20 (0.072 mg), sodium citrate (4.64 mg), sucrose (18 mg), and Water for Injection USP. Hydrochloric acid NF and/or sodium hydroxide NF are used to adjust the pH to 7.

Each cartridge delivers 600 International Units in 0.72 mL and the inactive ingredients: benzyl alcohol (7.2 mg; preservative), methionine (0.36 mg), polysorbate 20 (0.144 mg), sodium citrate (9.3 mg), sucrose (36 mg), and Water for Injection USP. Hydrochloric acid NF and/or sodium hydroxide NF are used to adjust the pH to 7.

Each cartridge delivers 900 International Units in 1.08 mL and the inactive ingredients: benzyl alcohol (10.8 mg; preservative), methionine (0.54 mg), polysorbate 20 (0.216 mg), sodium citrate (13.9 mg), sucrose (54 mg), and Water for Injection USP. Hydrochloric acid NF and/or sodium hydroxide NF are used to adjust the pH to 7.

Under current storage conditions, Follistim AQ may contain up to 11% of oxidized follitropin beta.

12 CLINICAL PHARMACOLOGY

12.1 Mechanism of Action

Women:

Follicle-stimulating hormone (FSH), the active component in Follistim AQ Cartridge, is required for normal follicular growth, maturation, and gonadal steroid production.

In women, the level of FSH is critical for the onset and duration of follicular development, and consequently for the timing and number of follicles reaching maturity. Follistim AQ Cartridge stimulates ovarian follicular growth in women who do not have primary ovarian failure. In order to effect the final phase of follicle maturation, resumption of meiosis and rupture of the follicle in the absence of an endogenous LH surge, human chorionic gonadotropin (hCG) must be given following treatment with Follistim AQ Cartridge when patient monitoring indicates appropriate follicular development parameters have been reached.

Men:

Follistim when administered with hCG stimulates spermatogenesis in men with hypogonadotropic hypogonadism. FSH, the active component of Follistim, is the pituitary hormone responsible for spermatogenesis.

12.3 Pharmacokinetics

Pharmacokinetic parameters for Follistim AQ Cartridge were evaluated in an open-label, single-center, randomized study in 20 healthy women. Serum FSH values from a single subcutaneous injection of reconstituted Follistim lyophilized powder administered by conventional syringe were compared to those values following a single subcutaneous injection of Follistim AQ Cartridge administered with the Follistim Pen injector. Administration of follitropin beta with the Follistim Pen resulted an 18% increase in AUC0–∞ and Cmax. The 18% difference in serum FSH concentrations resulting from administration of the two formulations was due to differences between the anticipated and actual volume delivered with the conventional syringe. The pharmacokinetic parameters for Follistim AQ Cartridge are as follows:

Table 5: Mean (SD) Pharmacokinetic Parameters of a Single Subcutaneous Injection of 150 IU of Follistim AQ Cartridge (n=20)
 | AUC0–∞ (IU/L*h) | Cmax (IU/L) | tmax (h) | t½ (h) | CLapp (L/h/kg)
Follistim AQ | 215.1 | 3.4 | 12.9 | 33.4 | 0.01
Cartridge | (45.8) | (0.7) | (6.2) | (4.2) | (0.003)
AUC0–∞ Area under the curve
Cmax Maximum concentration
tmax Time to maximum concentration
t½ Elimination half-life
CLapp Clearance

Absorption:

Women:

The bioavailability of Follistim following subcutaneous and intramuscular administration was investigated in healthy, pituitary-suppressed women given a single 300 international units dose. In these women, the area under the curve (AUC), expressed as the mean ± SD, was equivalent between the subcutaneous (455.6 ± 141.4 IU*h/L) and intramuscular (445.7 ± 135.7 IU*h/L) routes of administration. However, equivalence could not be established with respect to the peak serum FSH levels (Cmax). The Cmax achieved after subcutaneous administration and intramuscular administration was 5.41 ± 0.72 international units/L and 6.86 ± 2.90 international units/L, respectively. After subcutaneous or intramuscular injection the apparent dose absorbed was 77.8% and 76.4%, respectively.

The pharmacokinetics and pharmacodynamics of a single, intramuscular dose (300 international units) of Follistim were also investigated in a group (n=8) of gonadotropin-deficient, but otherwise healthy women. In these women, FSH (mean ± SD) AUC was 339 ± 105 international units*h/L, Cmax was 4.3 ± 1.7 international units/L. Cmax occurred at approximately 27 ± 5.4 hours after intramuscular administration.

A multiple dose, dose proportionality, pharmacokinetic study of Follistim was completed in healthy, pituitary-suppressed, female subjects given subcutaneous doses of 75, 150, or 225 international units for 7 days. Steady-state blood concentrations of FSH were reached with all doses after 5 days of treatment based on the trough concentrations of FSH just prior to dosing (Ctrough). Peak blood concentrations with the 75, 150, and 225 international units dose were 4.30 ± 0.60 international units/L, 8.51 ± 1.16 international units/L and 13.92 ± 1.81 international units/L, respectively.

Men:

No PK studies were conducted using Follistim AQ Cartridge in men. Exposures of follitropin beta from Follistim AQ Cartridge and Follistim are expected to be equivalent after adjusting for the 18% difference in dose [see Dosage and Administration (2)].

Serum levels of FSH were measured in a clinical study that compared the effects of two different dosing schedules of Follistim (150 international units three times a week or 225 international units twice a week) administered by subcutaneous injection concurrently with chorionic gonadotropin for induction of spermatogenesis in hypogonadotropic hypogonadal men. Administration of Follistim was started at Week 17. Mean serum trough concentrations of FSH remained fairly constant over the treatment period. At the end of treatment (Week 64), the mean serum trough concentrations of FSH were 2.09 international units/L in the 150 international units group and 3.22 international units/L in the 225 international units group. Serum trough concentrations of FSH measured prior to the first Follistim injection on the Mondays of active treatment period (Weeks 17 to 64) and one week after the end of treatment period are presented in Figure 1.

Figure 1: Mean (SD) Serum Trough Concentrations of FSH in Men Following Subcutaneous Administration of Follistim Using Two Different Dosing Schedules (150 International Units Three Times a Week or 225 International Units Twice a Week)

Distribution:

The volume of distribution of Follistim in healthy, pituitary-suppressed, women following intravenous administration of a 300 international units dose was approximately 8 L.

Metabolism:

The recombinant FSH in Follistim AQ Cartridge is biochemically very similar to urinary FSH and it is therefore anticipated that it is metabolized in the same manner.

Elimination:

The elimination half-life (t½) following a single subcutaneous injection of 150 IU of Follistim AQ Cartridge in women was 33.4 (4.2) hours. The clearance was 0.01 (0.003) L/h/kg.

Use in Specific Populations:

Body weight: The effect of body weight on the pharmacokinetics of Follistim was evaluated in a group of European and Japanese women who were significantly different in terms of body weight. The European women had a body weight of (mean ± SD) 67.4 ± 13.5 kg and the Japanese subjects were 46.8 ± 11.6 kg. Following a single intramuscular dose of 300 international units of Follistim, the AUC was significantly smaller in European women (339 ± 105 international units*h/L) than in Japanese women (544 ± 201 international units*h/L). However, clearance per kg of body weight was essentially the same for the respective groups (0.014 and 0.013 L/hr/kg).

Geriatric Use: The pharmacokinetics of Follistim has not been studied in geriatric subjects.

Pediatric Use: The pharmacokinetics of Follistim has not been studied in pediatric subjects.

Renal Impairment: The effect of renal impairment on the pharmacokinetics of Follistim has not been studied.

Hepatic Impairment: The effect of hepatic impairment on the pharmacokinetics of Follistim has not been studied.

13 NONCLINICAL TOXICOLOGY

13.1 Carcinogenesis, Mutagenesis, Impairment of Fertility

Long-term toxicity studies in animals have not been performed with Follistim to evaluate the carcinogenic potential of the drug. Follistim was not mutagenic in the Ames test using S. typhimurium and E. coli tester strains and did not produce chromosomal aberrations in an in vitro assay using human lymphocytes.

14 CLINICAL STUDIES

14.1 Ovulation Induction

The efficacy of Follistim for ovulation induction was evaluated in a randomized, assessor-blind, parallel-group comparative, multicenter safety and efficacy study of 172 chronic anovulatory women (105 subjects on Follistim) who had previously failed to ovulate and/or conceive during clomiphene citrate treatment. The study results for ovulation rates are summarized in Table 6 and those for pregnancy rates are summarized in Table 7.

Table 6: Cumulative Ovulation Rates
Cycle | Follistim (n=105)
First treatment cycle | 72%
Second treatment cycle | 82%
Third treatment cycle | 85%

Table 7: Cumulative Ongoing [All ongoing pregnancies were confirmed after at least 12 weeks after the hCG injection.] , [Study was not powered to demonstrate this outcome.] Pregnancy Rates
Cycle | Follistim (n=105)
First treatment cycle | 14%
Second treatment cycle | 19%
Third treatment cycle | 23%

14.2 Controlled Ovarian Stimulation as Part of an In Vitro Fertilization (IVF) or Intracytoplasmic Sperm Injection (ICSI) Cycle

The efficacy of Follistim AQ Cartridge was evaluated in a randomized, double-blind, active-controlled study of 1,509 healthy normal ovulatory women (mean age, body weight, and body mass index of 32 years, 68 kg and 25 kg/m^2, respectively) treated for one cycle with controlled ovarian stimulation and pituitary suppression with a GnRH antagonist as part of an in vitro fertilization or intracytoplasmic sperm injection cycle. This 2008 study was conducted in Europe and North America (United States and Canada). Approximately 54% of the subjects were from North America. The overall results, as well as the results from North America only, for clinical pregnancy are summarized in Table 8.

Table 8: Pregnancy Results from Treatment With Follistim AQ Cartridge and a GnRH Antagonist in Normal Ovulatory Women Undergoing Controlled Ovarian Stimulation as Part of an In Vitro Fertilization or Intracytoplasmic Sperm Injection Cycle. [Single treatment cycle results] Intent-to-Treat Population (ITT)
Parameter | Follistim AQ Cartridge Overall data (n=750) | Follistim AQ Cartridge North American data (n=403)
Clinical pregnancy rate/cycle initiation [Clinical pregnancy was assessed ≥6 weeks after transfer of one or two embryos.] | 41.1% | 48.9%

14.3 Induction of Spermatogenesis

The safety and efficacy of Follistim administered by subcutaneous injection concomitantly with chorionic gonadotropin for injection (hCG) has been examined in a multicenter, open-label, non-comparator clinical study for induction of spermatogenesis in hypogonadotropic hypogonadal men. The study compared the effects of two different Follistim dosing schedules on semen parameters and serum levels of follicle stimulating hormone (FSH). The multicenter study involved a 16-week pretreatment phase with urinary hCG at a dosage of 1,500 international units twice a week to normalize serum testosterone levels. If serum testosterone levels did not normalize after 8 weeks of hCG treatment, the urinary hCG dose could have been increased to 3,000 international units twice a week. This phase was followed by a 48-week treatment phase. Men who were still azoospermic after the pretreatment phase were randomized to receive either 225 international units Follistim together with 1,500 international units urinary hCG twice a week or 150 international units Follistim three times a week together with 1,500 international units urinary hCG twice weekly. Men who required 3,000 international units of urinary hCG twice a week in the pretreatment phase were continued on that dosage during the treatment phase. The mean age of patients in both treatment groups was approximately 30 years (range 18 to 47 years). At baseline, mean left and right testis volumes were 4.61 ± 2.94 mL and 4.57 ± 3.00 mL, respectively, in the group receiving three weekly injections of Follistim. For the group receiving two weekly injections of Follistim, the mean left and right testis volumes were 6.54 ± 2.45 mL and 7.21 ± 2.94 mL, respectively, at baseline. The primary efficacy endpoint was the percentage of patients with a mean sperm density of ≥1 × 10^6/mL on their last two treatment assessments. The outcomes of treatment in the 30 men enrolled in the treatment phase are summarized in Table 9.

Table 9: Number of Men Receiving Follistim Who Achieved a Mean Sperm Density of ≥10^6/mL on Their Last Two Treatment Assessments
 | Follistim 150 international units three times a week (n=15) |  | Follistim 225 international units twice a week (n=15) |  | Overall (n=30)
Sperm Density of ≥10^6/mL | n | % | n | % | n | %
Yes | 6 | 40 | 7 | 47 | 13 | 43
No | 9 | 60 | 8 | 53 | 17 | 57

Overall, the median time to reach a sperm concentration of 10^6 per mL was 165 days (range 25 to 327 days) in patients who demonstrated a sperm concentration of at least 10^6 per mL. The median time to reach a sperm concentration of at least 10^6 per mL was 186 days (range 25 to 327 days) for the 150 international units group and 141 days (range 43 to 204 days) for the 225 international units group. No pregnancy data were collected during the trial.

The local tolerance data were comparable between the two treatment groups. The mean percentage of days without pain calculated for all subjects in the treatment period was 91.3% for patients in the 150 international units (three times a week) and 76.0% for patients in the 225 international units (two times a week) Follistim treatment groups. In the 225 international units (twice per week) group, local symptoms judged as severe by the investigator were: itching in 1 patient (7%), pain in 2 patients (13%), bruising in 2 patients (13%), swelling in 2 patients (13%), and redness in 1 patient (7%). In the 150 international units (three times per week) group, 1 event in 1 patient (bruising, 7%) was judged as severe. No patient discontinued treatment due to injection site reaction or injection site pain.

16 HOW SUPPLIED/STORAGE AND HANDLING

Follistim AQ Cartridge (follitropin beta) injection is a clear and colorless solution in a disposable, prefilled single-patient-use glass cartridge with grey rubber piston and an aluminum crimp-cap with grey rubber inlay supplied in a box containing disposable, 29 gauge, ultra-fine, ½-inch, sterile BD Micro-Fine™ Pen Needles (for use with Follistim Pen available separately) and in the following presentations:

NDC 0052-0313-01 Follistim AQ Cartridge 300 international units per 0.36 mL with silver crimp-caps and 5 BD Micro-Fine Pen Needles

NDC 0052-0316-01 Follistim AQ Cartridge 600 international units per 0.72 mL with gold crimp-caps and 7 BD Micro-Fine Pen Needles

NDC 0052-0326-01 Follistim AQ Cartridge 900 international units per 1.08 mL with blue crimp-caps and 10 BD Micro-Fine Pen Needles

STORAGE AND HANDLING

Pharmacy Storage: Store refrigerated 2°C to 8°C (36°F to 46°F) until dispensed. Do not freeze.

Patient Storage: Store unused cartridge refrigerated at 2°C to 8°C (36°F to 46°F) until the expiration date, or at room temperature at up to 25°C (77°F) for 3 months or until expiration date, whichever occurs first. After first use, store at 2°C to 25°C (36°F to 77°F) and discard after 28 days. Store in the original carton to protect from light. Do not freeze.

17 PATIENT COUNSELING INFORMATION

Advise the patient to read the FDA-approved patient labeling (Patient Information).

Dosing and Use of Follistim AQ Cartridge with Pen

Instruct women and men on the correct usage and dosing of Follistim AQ Cartridge in conjunction with the Follistim Pen. Make sure that individuals who have used other gonadotropin products delivered by a syringe are aware of differences arising from use of the pen. Women and men should read and follow all instructions in the Follistim Pen "Instructions for Use" Manual prior to administration of Follistim AQ Cartridge.

Advise women and men of the number of doses which can be extracted from the full unused Follistim AQ Cartridge that you have prescribed.

Therapy Duration and Necessary Monitoring in Women and Men Undergoing Treatment

Prior to beginning therapy with Follistim AQ Cartridge, inform women and men about the time commitment and monitoring procedures necessary to undergo treatment [see Dosage and Administration (2), Warnings and Precautions (5.10)].

Instructions on a Missed Dose

Inform women and men that if they miss or forget to take a dose of Follistim AQ Cartridge, the next dose should not be doubled and they should call the healthcare provider for further dosing instructions.

Ovarian Hyperstimulation Syndrome

Inform women regarding the risks with use of Follistim AQ Cartridge of Ovarian Hyperstimulation Syndrome [see Warnings and Precautions (5.2)] and associated symptoms including lung and blood vessel problems [see Warnings and Precautions (5.3)] and ovarian torsion [see Warnings and Precautions (5.4)].

Multi-fetal Gestation and Birth

Inform women regarding the risk of multi-fetal gestations with the use of Follistim AQ Cartridge [see Warnings and Precautions (5.5)].

Manufactured for: Merck Sharp & Dohme Corp., a subsidiary of
MERCK & CO., INC., Whitehouse Station, NJ 08889, USA

Manufactured by:
Organon USA Inc., a subsidiary of Merck & Co., Inc.
2000 Galloping Hill Road
Kenilworth, NJ 07033
U.S. License No. 2193

BD, BD Logo and BD Micro-Fine are trademarks of Becton, Dickinson and Company.

For patent information: www.msd.com/research/patent

Copyright © 2004-2023 Merck Sharp & Dohme B.V., a subsidiary of Merck & Co., Inc.
All rights reserved.

uspi-mk8328-SOi-2303r015

PATIENT INFORMATION

Follistim® (Fol'-lis-tim) AQ Cartridge
(follitropin beta) injection
for subcutaneous use

Read this Patient Information before you start using Follistim® AQ Cartridge and each time you get a refill. There may be new information. This information does not take the place of talking with your healthcare provider about your medical condition or treatment.

What is Follistim AQ Cartridge?

Follistim AQ is a prescription medicine that contains follicle-stimulating hormone (FSH). The medicine is taken with the Follistim Pen®.

Follistim AQ Cartridge is used:

In women:

- to help healthy ovaries to develop (mature) and release eggs
- as part of treatment programs that use special techniques (skills) to help women get pregnant by causing their ovaries to produce more mature eggs

In men:

- to help bring about the production and development of sperm

Who should not use Follistim AQ Cartridge?

Do not start using Follistim AQ Cartridge if you are a Woman or Man who:

- is allergic to recombinant human FSH products
- has a high level of FSH in your blood indicating that your ovaries (women only) or testes (men only) may be permanently damaged and do not work at all
- has uncontrolled thyroid, pituitary, or adrenal gland problems
- is allergic to streptomycin or neomycin (types of antibiotics)
- has a tumor of the hypothalamus, pituitary gland, breast, uterus (women only), ovary (women only), or testis (men only)

Do not start using Follistim AQ Cartridge if you are a Woman who:

- is pregnant or think you may be pregnant
- has heavy or irregular vaginal bleeding and the cause is not known
- has ovarian cysts or enlarged ovaries, not due to polycystic ovary syndrome (PCOS)

Talk to your healthcare provider before taking this medicine if you have any of the conditions listed above.

Before you use Follistim AQ, tell your healthcare provider about all of your medical conditions, including if you:

- have an increased risk of blood clots (thrombosis)
- have ever had a blood clot (thrombosis), or anyone in your immediate family has ever had a blood clot (thrombosis)
- had stomach (abdominal) surgery
- had twisting of your ovary (ovarian torsion)
- had or have a cyst in your ovary
- have polycystic ovary disease
- have any other medical conditions
- are breastfeeding or plan to breastfeed. It is not known if the medicine in Follistim AQ Cartridge passes into your breast milk. You and your healthcare provider should decide if you will take Follistim AQ Cartridge or breastfeed. You should not do both.

Tell your healthcare provider about all the medicines you take, including prescription and non-prescription medicines, vitamins, and herbal supplements. Some medicines may affect how Follistim AQ Cartridge works. Follistim AQ Cartridge may also affect how your other medicines work. Keep a list of your medicines and show it to your healthcare provider and pharmacist when you get a new medicine.

How should I use Follistim AQ Cartridge?

- Be sure that you read, understand, and follow the "Patient Instructions for Use" that come with Follistim AQ Cartridge.
- Use Follistim AQ Cartridge exactly as your healthcare provider tells you to.
- Your healthcare provider will tell you how much Follistim AQ Cartridge to use, how to inject it, and how often it should be injected.
- Do not inject Follistim AQ Cartridge at home until your healthcare provider has taught you the right way to put the cartridge and pen device together and to inject yourself.
- Do not mix any other medicines into the cartridge.
- Do not change your dose of Follistim AQ Cartridge unless your healthcare provider tells you to.
- Call your healthcare provider immediately if you use too much Follistim AQ Cartridge.
- If you miss or forget to take a dose, do not double your next dose. Ask your healthcare provider for instructions.
- Use Follistim AQ Cartridge only with the Follistim Pen.
- Do not use the Follistim Pen if you are blind or visually impaired unless you have assistance from an individual with good vision who is trained in the right way to use the pen.
- Do not re-use the BD Micro-Fine™ Pen Needle.
- Your healthcare provider will do blood and urine hormone tests while you are taking Follistim AQ Cartridge. Make sure you follow-up with your healthcare provider to have your blood and urine tested when told to do so.

Women:

- Your healthcare provider may do ultrasound scans of your ovaries. Make sure you follow-up with your healthcare provider to have your ultrasound scans.

Men:

- Your healthcare provider may test your semen while you are taking Follistim AQ Cartridge. Make sure you follow-up with your healthcare provider to give a semen sample for testing.

What are the possible side effects of Follistim AQ Cartridge?

Side effects are grouped by how serious they are and how often they may happen.

Serious side effects include:

In women:

- Ovarian enlargement
- Ovarian hyperstimulation syndrome (OHSS). OHSS is a serious medical problem that can happen when the ovaries are over stimulated. In rare cases it has caused death. OHSS causes fluid to build up suddenly in your stomach and chest areas and can cause blood clots to form.
- Lung problems. Follistim AQ Cartridge can cause you to have fluid in your lungs (atelectasis) and trouble breathing (acute respiratory distress syndrome).
- Blood clots. Follistim AQ Cartridge may increase your chance of having blood clots in your blood vessels. Blood clots can cause:
  - blood vessel problems (thrombophlebitis)
  - stroke
  - loss of your arm or leg
  - blood clot in your lungs (pulmonary embolus)
  - heart attack
- Ovarian torsion. Follistim AQ Cartridge may increase the chance of twisting of the ovaries in women with certain conditions such as OHSS, pregnancy and previous abdominal surgery. Twisting of the ovary could cause the blood flow to the ovary to be cut off.
- Pregnancy and birth of multiple babies. Having a pregnancy with more than one baby at a time increases the health risk for you and your babies. Discuss your chances of multiple births with your healthcare provider.
- Birth defects. A woman's age, certain sperm problems, genetic background of both parents and a pregnancy with multiple babies can increase the chance that your baby might have birth defects.
- Ectopic pregnancy (pregnancy outside of the womb). The chance of a pregnancy outside of the womb is increased in women with damaged fallopian tubes.
- Miscarriage. The chance of loss of an early pregnancy may be increased in women who have difficulty with becoming pregnant at all.

Call your healthcare provider right away if you develop any of the following:

- pain in your lower stomach area
- nausea
- vomiting
- weight gain
- diarrhea
- decreased urine output
- trouble breathing
- any other unusual symptoms that concern you

The most common side effects of Follistim AQ Cartridge include:

In women:

- headache
- nausea
- stomach pain
- discomfort or pain in the lower stomach area
- cyst (closed sac) in the ovary
- feeling tired

In men:

- headache
- pain at the injection site
- bruising, swelling or redness at the injection site
- breast enlargement
- acne
- testicular cyst

These are not all the possible side effects of Follistim AQ Cartridge. For more information, ask your healthcare provider or pharmacist.

Call your healthcare provider immediately if you get worsening or strong pain in the lower stomach area (abdomen). Also, call your healthcare provider immediately if this happens some days after the last injection has been given.

Tell your healthcare provider if you have any side effect that bothers you or that does not go away.

Call your doctor for medical advice about side effects. You may report side effects to FDA at 1-800-FDA-1088.

How should I store Follistim AQ Cartridge?

- Store Follistim AQ Cartridge in the refrigerator between 2°C to 8°C (36°F to 46°F) until the expiration date.
- Follistim AQ can be stored at or below 25°C (77°F) for 3 months or until the expiration date, whichever comes first. Once the rubber inlay of the Follistim AQ Cartridge has been pierced by a needle, the product may be stored only for a maximum of 28 days at 2°C to 25°C (36°F to 77°F).
- Keep Follistim AQ Cartridge away from light.
- Do not freeze.

Keep Follistim AQ Cartridge and all medicines out of the reach of children.

General information about Follistim AQ Cartridge

Medicines are sometimes prescribed for purposes other than those listed in the Patient Information leaflet. Do not use Follistim AQ for a condition for which it was not prescribed. Do not give Follistim AQ Cartridge to other people, even if they have the same condition that you have. It may harm them.

This Patient Information leaflet summarizes the most important information about Follistim AQ Cartridge. If you would like more information, talk with your healthcare provider. You can ask your pharmacist or healthcare provider for more information about Follistim AQ Cartridge that is written for healthcare professionals.

For more information, go to www.follistim.com or call 1-866-836-5633.

What are the ingredients in Follistim AQ Cartridge?

Active ingredient: follitropin beta

Inactive ingredients: benzyl alcohol NF-10 mg/mL (preservative), methionine, polysorbate 20, sodium citrate, sucrose, Water for Injection. Hydrochloric acid and/or sodium hydroxide are used to adjust the pH.

Manufactured for: Merck Sharp & Dohme Corp., a subsidiary of
MERCK & CO., INC., Whitehouse Station, NJ 08889, USA

Manufactured by:
Organon USA Inc., a subsidiary of Merck & Co., Inc.
2000 Galloping Hill Road
Kenilworth, NJ 07033
U.S. License No. 2193

BD, BD Logo and BD Micro-Fine are trademarks of Becton, Dickinson and Company.

For patent information: www.msd.com/research/patent

Copyright © 2004-2023 Merck Sharp & Dohme B.V., a subsidiary of Merck & Co., Inc.
All rights reserved.

Revised: 3/2023

usppi-mk8328-SOi-2303r016

PATIENT INSTRUCTIONS FOR USE

Follistim® (Fol΄-lis-tim) AQ Cartridge
(follitropin beta) injection
for subcutaneous use

Read the Patient Instructions for Use that comes with Follistim® AQ Cartridge before you start using it and each time you get a refill. There may be new information. This information does not take the place of talking with your healthcare provider about your medical condition or treatment.

A. Getting Ready
  - Follistim Pen is not recommended for the blind or visually impaired user without the assistance of an individual with good vision, trained in the proper use of the injection device.
  - Learn about all of the parts of the Follistim Pen (See Figure 1), Follistim AQ Cartridge (See Figure 2) and the BD Micro-Fine™ Pen Needle (See Figure 3). You will need to recognize these parts to follow the directions.
    Figure 1. Follistim Pen and its Parts
    Figure 2. Parts of Follistim AQ Cartridge
    Figure 3. Parts of BD Micro-Fine Pen Needle Unit
  - Remove the Cartridge out of the refrigerator.
  - Injecting cold drug is likely to cause discomfort. Allow the drug to reach room temperature before taking the injection.
  - Check the liquid in the cartridge to make sure it is clear and colorless. If the solution is not clear and colorless or has particles in it, do not use it.
  - Gather the supplies you will need for your injection. You will need:
    - a clean dry surface
    - alcohol
    - cotton balls or alcohol pads
    - sterile gauze
    - a puncture-proof container to throw away the used syringe and needle
  - Wash your hands with soap and water and dry them before you use Follistim Pen or when you replace the cartridge.
B. Loading the Follistim Pen with the Follistim AQ Cartridge
  - Holding the Pen Body firmly with one hand, pull off the Protective Cap with your other hand (See Figure 4). Put the cap aside on a clean, dry surface.
    Figure 4
  - Unscrew the entire Pen Body from the Cartridge Holder (See Figure 5). Place the Cartridge Holder and the Pen Body aside on a clean, dry surface.
    Figure 5
  - Take the Follistim AQ Cartridge out of its package. Clean the rubber inlay on the cartridge with an alcohol pad. Pick up the Cartridge Holder. Put the Cartridge into the Cartridge Holder (See Figure 6). The metal rimmed cap goes in first.
    Figure 6
  - Pick up the Pen Body and lower it into the Cartridge Holder. The black rod must press against the Rubber Piston on the cartridge. Screw the Pen Body fully onto the Cartridge Holder (See Figure 7). Make sure there is no gap between the Pen Body and the Cartridge Holder. The arrow () on the Cartridge Holder should point to the middle of the yellow alignment mark () on the blue Pen Body.
    Figure 7
  - Clean the open end of the Cartridge Holder with an alcohol pad (See Figure 8).
    Figure 8
  - Pick up a new BD Micro-Fine Pen Needle that is in its Outer Needle Shield. Peel off the protective paper seal (See Figure 9). Do not touch the needle. Do not place the open needle on any surface. Use Only the BD Micro-Fine 0.33 mm × 12.7 mm (29G) Pen Needles as supplied with the Follistim AQ Cartridge.
  - You must use a new BD Micro-Fine Pen Needle with each injection. Never reuse a needle. Attach a new BD Micro-Fine Pen Needle after you make sure there is a Follistim AQ Cartridge in the Cartridge.
    Figure 9
  - Hold the Outer Needle Shield firmly in one hand while holding the Cartridge Holder firmly in the other hand. Push the end of the Cartridge Holder into the Outer Needle Shield. Screw them tightly together (See Figure 10). Place your Follistim Pen with the loaded cartridge and attached needle, flat on a clean, dry surface.
    Figure 10
C. Preparing the Injection Site
  - Follistim AQ Cartridge can be injected directly into a layer of fat under your skin (subcutaneously).
  - When giving a subcutaneous injection, follow your healthcare provider's instructions about changing the site for each injection. This will help lower your chances of having a skin reaction.
  - Do not inject Follistim AQ Cartridge into an area that is tender, red, bruised, or hard.
  - The recommended sites for injecting Follistim AQ Cartridge subcutaneously are:
    - just below your belly button (navel) (See Figure 11)
      Figure 11
    - the upper outer area of your thigh (See Figure 12)
      Figure 12
  - Clean the skin with an alcohol wipe where the injection is to be made. Clean about two inches around the injection site where the needle will be inserted. Do not touch the cleaned area of skin.
D. Dialing the Dose Before You Give the Injection
  - Your healthcare provider will decide on the dose of Follistim AQ Cartridge to be given. This dose may be increased or decreased as your treatment progresses depending on your individual type of treatment.
  - Follistim AQ Cartridge using Follistim Pen can be administered subcutaneously (beneath the skin) in prescribed doses from 50 International Units (IU) up to 450 IU, in marked 25 IU increments. The Dosage Scale on the Pen has numbers and audible clicks to help you set the correct dose.
  - Pull off the outer needle shield. Leave the Inner Needle Shield in place over the needle attached to the Pen (See Figure 13). Do not throw the Outer Needle Shield away, you will need it later when you throw the needle away.
    Figure 13
  - Carefully remove the Inner Needle Shield and discard it (See Figure 14). Do not touch the needle or let it touch any surface while uncapped.
    Figure 14
  - Hold the Follistim Pen with the needle pointing upwards. Tap the Cartridge Holder gently with your finger to help air bubbles rise to the top of the needle. The small amount of air bubble will not affect the amount of medicine you receive.
  - With a loaded new, unused cartridge:
    1. Dial the Dosage Knob until you hear one click. With the needle pointing upwards, push in the Injection Button.
    2. Look for a droplet at the tip of the needle (See Figure 15). If you see the droplet, then you can dial in your dose.
    3. If you do not see a droplet, repeat Step 1 (as above) until you see droplet.
      You must make sure you see a droplet of medicine (check the flow of medicine) or you may not inject the correct amount of medicine.
      Figure 15
  - With a partially used cartridge, to give yourself another dose of medicine you will need to attach a new BD Micro-Fine Pen Needle and look for a droplet forming at the tip of the needle (See Figure 15 above). If you see a droplet, then you can dial in your dose.
    If no droplet:
    1. Dial the Dosage Knob until you hear one click. With the needle pointing upwards, push in the Injection Button.
    2. Look for a droplet at the tip of the needle. If you see the droplet, then you can dial in your dose.
  - Your Follistim AQ Cartridge should be one of the following:
    - Silver Metal Cap – 300 international units
    - Gold Metal Cap – 600 international units
    - Blue Metal Cap – 900 international units
    If you did not understand that you should have one of the cartridges above, please contact your healthcare provider.
  - For doses of 50 IU up to 450 IU, turn the Dosage Knob until the correct dosage aligns with the dosage markers on each side of the Dosage Window (see Figure 16).
    Figure 16
  - If by mistake you dial past the correct number, do not try to turn the Dosage Knob backward to fix the mistake. Continue to turn the Dosage Knob in the same direction past the 450 IU mark, as far as it will turn. The Dosage Scale must move freely. Push the Injection Button in all the way. See Figure 17. Start to dial again starting from "0" upwards. By following these directions, you will not lose any medicine from the Follistim AQ Cartridge (See "Checking the Medicine Level Remaining").
    Figure 17
    - If you turn the Dosage Knob backward to correct the mistake, it will not damage the Pen, but you will lose some medication from the Follistim AQ Cartridge.
    - Never dial your dose or try to correct a dialing mistake when the needle is still in your skin as this may result in your receiving an incorrect dose.
    - If your prescribed dose exceeds the deliverable dose of Follistim Pen or exceeds the amount remaining in the cartridge, you will need to give yourself more than one injection.
E. Giving Yourself an Injection
  - Pinch a fold of skin at the cleaned injection site. Do not touch the cleaned area of skin.
  - With the other hand hold the entire Pen with Cartridge loaded and Needle on like you would a pencil. Use a quick "dart-like" motion to insert the needle straight up and down (90-degree angle).
  - Press the injection button all the way in to make sure you give yourself a full injection. (See Figure 18). Wait for five seconds before pulling the needle out of the skin. The middle of the Dosage Window should display a dot next to the "0".
    Figure 18
    If the injection button does not push in all the way, and the number in the Dosage Window does not read "0", it means there is not enough medication left in the cartridge to complete your prescribed dose. The number in the Dosage Window will give you the amount of medicine needed to complete your dose. Write this number down. This will be the number you dial for the completion of your dose. Start over with a new Follistim AQ Cartridge and a new needle and follow all the instructions up to this step. Make sure you choose a different injection site to complete your dose of Follistim AQ Cartridge.
  - Pull out the BD Micro-Fine Needle and firmly press down on the injection site with an alcohol swab. Use the BD Micro-Fine Pen Needle for one injection only.
  - Place the Outer Needle Shield on a flat table surface with the opening pointing up. The opening of the Outer Needle Shield is the wider end with the rim. Without holding on to the Outer Needle Shield, carefully insert the needle (attached to the Follistim Pen) into the opening of the Outer Needle Shield and push down firmly. The Outer Needle Shield should now be attached to the Cartridge Holder and covering the needle (See Figure 19).
    Figure 19
  - Grip the Outer Needle Shield and use it to unscrew the needle from the Cartridge Holder (See Figure 20). If there is Follistim AQ Cartridge medicine left for more injections, put the Pen Cap back on the Pen Body and store your Follistim Pen in a safe place in the refrigerator (not in the freezer) or at room temperature. Never store the Follistim Pen with a needle attached to it. If you are giving an injection to another person, be very careful when removing the needle from the skin. Accidental needle sticks can transmit potentially serious or grave infectious diseases.
    Figure 20
  - Throw away the Outer Needle Shield with the used needle right away. Do not throw away in a trash can. Place it in a "special" container. (See "How Do I Throw Away Used Cartridges and Needles?")
  - If there is Follistim AQ Cartridge medicine left for more injections, put the Pen Cap back on the Pen Body and store your Follistim Pen in a safe place in the refrigerator (not in the freezer) or at room temperature. Never store the Follistim Pen with a needle attached to it. If you are giving an injection to another person, be very careful when removing the needle from the skin. Accidental needle sticks can lead to serious infections.
  - Unscrew the Pen Body from the Cartridge Holder with the empty Follistim AQ Cartridge (See Figure 21).
    Figure 21
  - Put the Pen Body down on a clean, dry surface and remove the empty Follistim AQ Cartridge from the Cartridge Holder (See Figure 22). Safely, dispose of the empty Follistim AQ Cartridge right away in the same "special" container that you used for the needle disposal. Do not put the cartridge in a trash can. At the end of your treatment cycle, your doctor can advise you on how to properly dispose of the container. (See "How Do I Throw Away Used Cartridges and Needles?")
    Figure 22
F. Checking the Medicine Level Remaining
  For women and men:
  Have your healthcare provider advise you of the number of prescribed doses which can be extracted from the full unused Follistim AQ Cartridge.
  - Do not use the cartridge beyond the advised number of doses. Otherwise, you will run the risk that there will not be enough volume of drug for your prescribed dose.
  For women only:
  - Keep a Follistim Pen Treatment Diary as follows:
    1. Record the Follistim AQ Cartridge content on Day 1. This will either be 300, 600 or 900 international units depending on what your healthcare provider has prescribed for you.
    2. Record the dose you have been prescribed for your injection.
    3. Subtract your Day 1 dose from the Follistim AQ Cartridge content (300, 600 or 900 international units). (See example – Figure 23.) This will give you the remaining Follistim AQ Cartridge content after the Day 1 dose is taken.
    4. Place the number determined as the content after Day 1 (see number 3) in the box as the Follistim AQ Cartridge content available for Day 2. (See example – Figure 23.)
    5. Subtract your Day 2 dose from the Follistim AQ Cartridge content you recorded in Step 4. This will give you the remaining Follistim AQ Cartridge content after Day 2. Record this number of units. (See example – Figure 23.)
    6. Repeat the steps to determine the Follistim AQ Cartridge content available and Follistim AQ Cartridge remaining for each day of use.
      Figure 23. Example of Treatment Diary Starting with a 600 International Unit Cartridge
  If you do not know if there is not enough medicine left in the Follistim AQ Cartridge for your next prescribed dose, see section "If There is Not Enough Follistim AQ in the Cartridge".
G. If There is Not Enough Follistim AQ in the Cartridge
  1. If you realize before you inject that you do not have enough medicine remaining in your Follistim AQ Cartridge for your complete dose, follow either Option 1 or Option 2, but not both.
    - Option 1:
      - Dial your dose and inject the remaining content in the Follistim AQ Cartridge. The Dosage Knob Injection Button will not push in all the way (do not try to force down the button) and the Dosage Window number will not read "0" but will read the number of units you will need to complete your prescribed dose.
      - Write down the number of units needed to complete your dose.
      - Remove the needle and dispose of it properly (see "How Do I Throw Away Used Cartridges and Needles?").
      - Using the Dosage Knob, reset the Dial Window to "0" by turning the Dosage Knob past the 450 IU mark as far as it will turn and push the Injection Button in all the way.
      - Before attempting to replace a Follistim AQ Cartridge, be sure that a BD Micro-Fine Pen Needle is not attached to the Follistim Pen.
      - Insert a new cartridge into the Follistim Pen and attach a new BD Micro-Fine needle.
      - Dial to the number of units you have written down to complete your prescribed dose.
      - Prepare a different injection site and inject the remaining drug to complete your dose (See "Giving Yourself an Injection").
    - Option 2
      - Remove the Follistim AQ Cartridge.
      - Start over with a new Follistim AQ Cartridge and Insert into the Follistim Pen.
      - Follow the instructions for "Dialing the Dose" and "Giving Yourself an Injection."
  2. If you realize after you have inserted the needle at the injection site that you do not have enough medicine remaining in your Follistim AQ Cartridge for your complete dose:
    - Inject the remaining content in the Follistim AQ Cartridge. The Injection Button will not push in all the way and the number in the Dosage Window will not read "0" but will read the number of units you will need to complete your prescribed dose.
    - Wait 5 seconds before withdrawing the needle from your skin and gently apply pressure to the injection site with an alcohol pad.
    - Dispose of the used needle (See "How Do I Throw Away Used Cartridges and Needles?").
    - Write down the number of units needed to complete your dose.
    - Using the Dosage Knob, reset the Dial Window to "0" by turning the Dosage Knob past the 450 IU mark as far as it will turn and push the Injection Button in all the way.
    - Insert a new cartridge into the Follistim Pen and attach a new BD Micro-Fine needle.
    - Dial to the number you have recorded to complete your prescribed dose.
    - Prepare a different injection site and inject the remaining drug to complete your dose (See "Giving Yourself an Injection").
H. How to Solve Problems with Follistim AQ Cartridge and Follistim Pen
  If you have problems with using the Follistim AQ Cartridge and the Follistim Pen, see the following chart. If you still have problems after following the chart or if your problem is not on the chart, contact your healthcare provider.

PROBLEM | POSSIBLE CAUSES | WHAT TO DO
The Pen Body will not screw tightly into the Cartridge Holder. | Is something in the way? | Take out the Follistim Cartridge and check the Cartridge Holder to see if anything is in the way. Follow the instructions in this pamphlet to Screw the Pen Body fully onto the Cartridge Holder.
No drug is coming out while checking the flow. | The Cartridge Holder and the Pen Body are not properly screwed together. | Remove the current needle; tighten the Pen Body to the Cartridge Holder ensuring the arrow on the Cartridge Holder is pointing to the middle of the yellow alignment mark on the blue Pen Body. Attach a new needle to the Pen. Recheck the flow as follows:; 1. Dial the Dosage Knob until you hear one click. With needle pointing upwards, push in the Injection Button. 2. Look for a droplet at the tip of the needle.
No drug is coming out while checking the flow. | Is the Follistim Cartridge empty? | Change to a new cartridge.
No drug is coming out while checking the flow. | Has the needle been properly attached to the Follistim Pen? | Remove needle and replace with a new one, ensuring that the needle is screwed on tightly to the Pen. Recheck the flow as follows:; 1. Dial the Dosage Knob until you hear one click. With needle pointing upwards, push in the Injection Button. 2. Look for a droplet at the tip of the needle.
You are concerned that you can turn the Dosage Knob to the next number without clicking and the injection button spins freely. | This is not a problem. | The system is in the reset mode. The Injection Button and Dosage Knob must be pushed all the way down to '0' to re-engage the mechanism and the correct dose can now be set. A click will be heard for each setting in the viewing window.
The Dosage Knob does not go back to '0' while you are injecting. | Is the Follistim Cartridge empty? | Change to a new cartridge.
The Dosage Knob does not go back to '0' while you are injecting. | Is the needle blocked? | 1. Remove the needle from the skin and dispose of safely. 2. Check the Dosage Window and note how much remaining drug to inject. 3. Attach a new needle.; Recheck the flow as follows:; 1. Dial the Dosage Knob until you hear one click. With needle pointing upwards, push in the Injection Button. 2. Look for a droplet at the tip of the needle. 3. Dial remaining dose.
Some of the drug is dripping out of the needle when you withdraw it from your skin. | Did you take the needle out of your skin before waiting 5 seconds as directed in Step 15? | If this happens you should inform your doctor. To avoid this problem again, you should always wait 5 seconds after you push the Injection Button before you withdraw the needle from your skin.
The needle is left on the Follistim Pen. | Have you missed any of the instructions? | Dispose of the needle in a properly secured container as instructed by your doctor. Change to a new Follistim Cartridge and a new needle.
After your last injection, a remaining volume may be left in the cartridge in addition to the normal quantity of drug dispensed. | The cartridge contains extra volume for checking the drug flow. | This is not a problem.
You cannot get the cartridge out of the Follistim Pen. | Is the needle attached? | Remove the needle from the Follistim Pen and dispose of properly. (Unscrew the Cartridge Holder from the Pen Body and take out the cartridge.)
You are not sure how much drug is left in the cartridge, and you do not want to start an injection and then find out that there is not enough drug. | Have you kept good records of your doses? | In case of any doubt, you should load a new, unused Follistim Cartridge into the Follistim Pen. See "If There is Not Enough Follistim AQ in the Cartridge." To avoid this problem again, you should record your injections. (Women should use a treatment diary.)

Important: If you have a question, always mention the Lot number of your Follistim Pen as printed on the Pen Body. If you have a complaint, please do not discard any product or packaging.

For questions on information contained in this leaflet, call 1-866-836-5633.

www.follistim.com

How Do I Throw Away Used Cartridges and Needles?

Check with your healthcare provider or pharmacist for instructions about the right way to throw away used cartridges and needles. There may be special local or state laws about how to throw away used syringes and needles.
  - Do not throw away used cartridges and needles in the household trash and do not recycle them.
  - Put used and empty cartridges and needles in a closeable, puncture-resistant container. You may use a sharps container (such as a red bio-hazard container), a hard plastic container with a screw-on cap (such as an empty detergent bottle) or in a metal container with a plastic lid, (such as a coffee can).
  - When the container is full, tape around the cap or lid to make sure the cap or lid does not come off.
  - When your injection is given by another person, this person must also be careful when removing the cartridge and needle and disposing of the cartridge and needle to prevent accidental needle stick injury and passing infection.

How Do I Care for the Follistim Pen?

1. Clean all exposed surfaces of the Follistim Pen with a clean, damp cloth such as a paper towel. Never wash it in water, detergent or strong medical cleaners.
2. Handle the Follistim Pen carefully to avoid causing damage. You could damage the Follistim Pen by dropping it or handling it roughly.
3. Keep the Follistim Pen away from dust and dirt.
4. Never store the Follistim Pen with a needle attached to it. If you store the Follistim Pen with the needle attached, the drug could leak out and there is risk of contamination.
5. If the Follistim Pen breaks or is damaged, do not try to fix it yourself. Contact your healthcare provider.
6. Do not share your Follistim Pen with another person.

How should I store Follistim AQ Cartridge?

- Store Follistim AQ Cartridge in the refrigerator between 2°C to 8°C (36°F to 46°F) until the expiration date.
- Follistim AQ can be stored at or below 25°C (77°F) for 3 months or until the expiration date, whichever comes first. Once the rubber inlay of the Follistim AQ Cartridge has been pierced by a needle, the product may be stored only for a maximum of 28 days at 2°C to 25°C (36°F to 77°F).
- Keep Follistim AQ Cartridge away from light.
- Do not freeze.

Keep Follistim AQ Cartridge, needles, and the disposal container, out of the reach of children.

Manufactured for: Merck Sharp & Dohme Corp., a subsidiary of
MERCK & CO., INC., Whitehouse Station, NJ 08889, USA

Manufactured by:
Organon USA Inc., a subsidiary of Merck & Co., Inc.
2000 Galloping Hill Road
Kenilworth, NJ 07033
U.S. License No. 2193

BD, BD Logo and BD Micro-Fine are trademarks of Becton, Dickinson and Company.

For patent information: www.msd.com/research/patent

Copyright © 2004-2023 Merck Sharp & Dohme B.V., a subsidiary of Merck & Co., Inc.
All rights reserved.

Revised: 3/2023

usppi-mk8328-SOi-2303r016

PACKAGE LABEL

PRINCIPAL DISPLAY PANEL - 300 IU Kit Carton

NDC 0052-0313-01

Rx only

Follistim® AQ Cartridge 300 IU
(follitropin beta) injection

For use only with Follistim Pen®,
available separately

For Subcutaneous Use
For Single Patient Use Only

Contents:
1 Sterile Prefilled Cartridge containing 0.36 mL Follistim®
5 BD Micro-Fine™ Pen Needles

Dispense with Full Prescribing Information

PACKAGE LABEL

PRINCIPAL DISPLAY PANEL - 600 IU Kit Carton

NDC 0052-0316-01

Rx only

Follistim® AQ Cartridge 600 IU
(follitropin beta) injection

For use only with Follistim Pen®,
available separately

For Subcutaneous Use
For Single Patient Use Only

Contents:
1 Sterile Prefilled Cartridge containing 0.72 mL Follistim®
7 BD Micro-Fine™ Pen Needles

Dispense with Full Prescribing Information

PACKAGE LABEL

PRINCIPAL DISPLAY PANEL - 900 IU Kit Carton

NDC 0052-0326-01

Rx only

Follistim® AQ Cartridge 900 IU
(follitropin beta) injection

For use only with Follistim Pen®,
available separately

For Subcutaneous Use
For Single Patient Use Only

Contents:
1 Sterile Prefilled Cartridge containing 1.08 mL Follistim®
10 BD Micro-Fine™ Pen Needles

Dispense with Full Prescribing Information